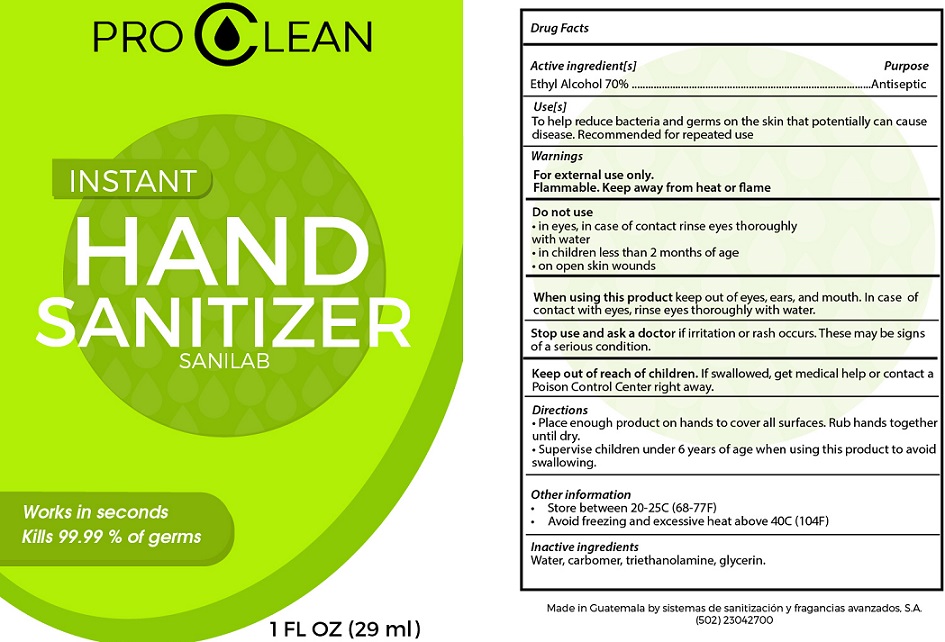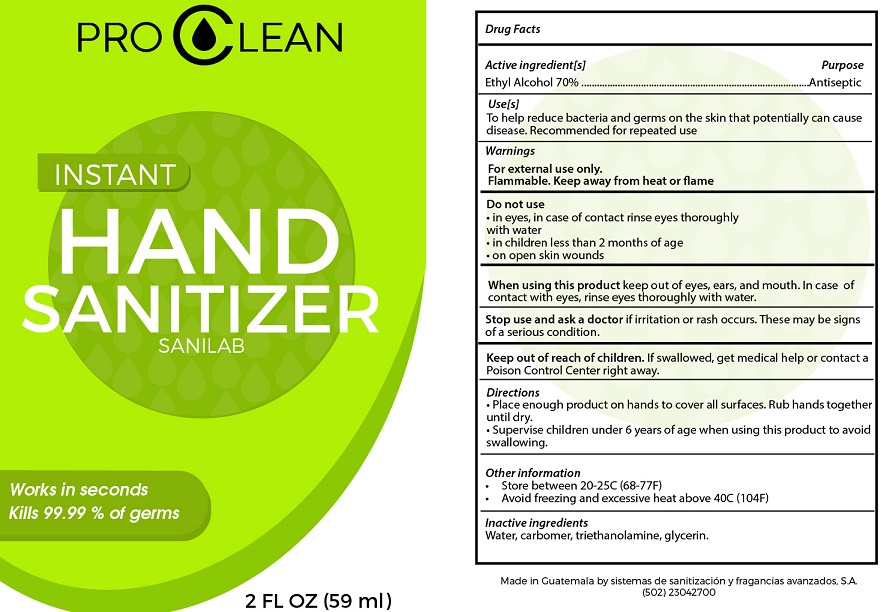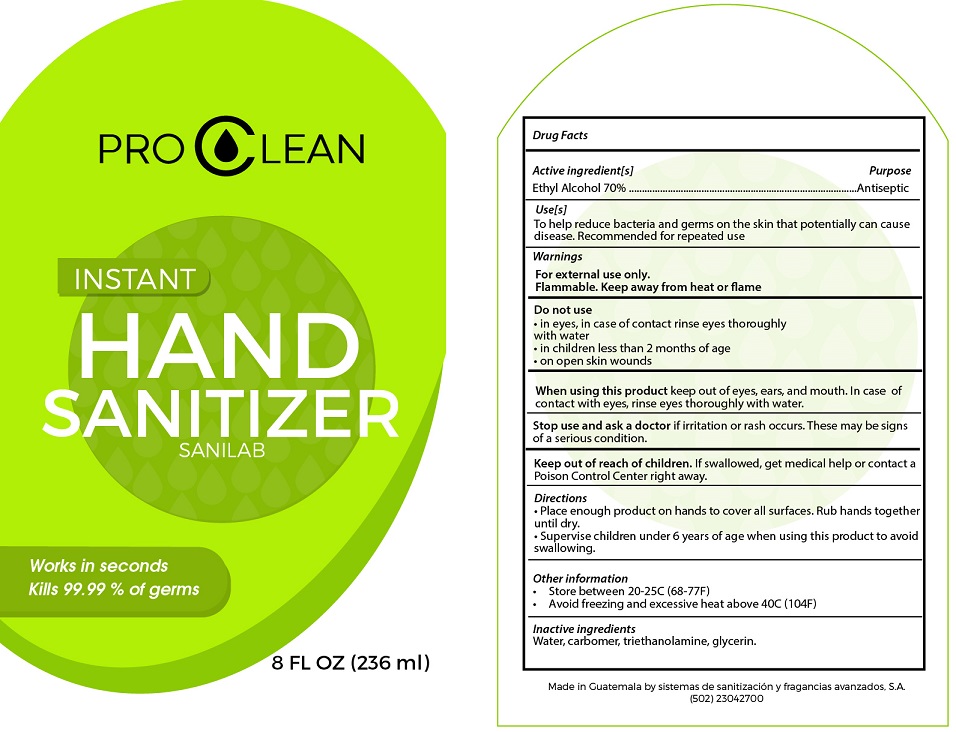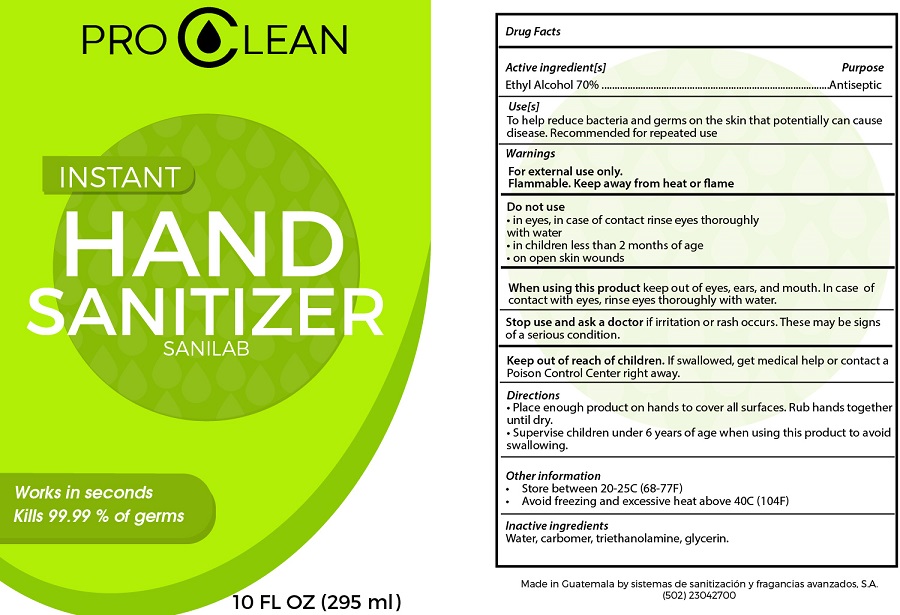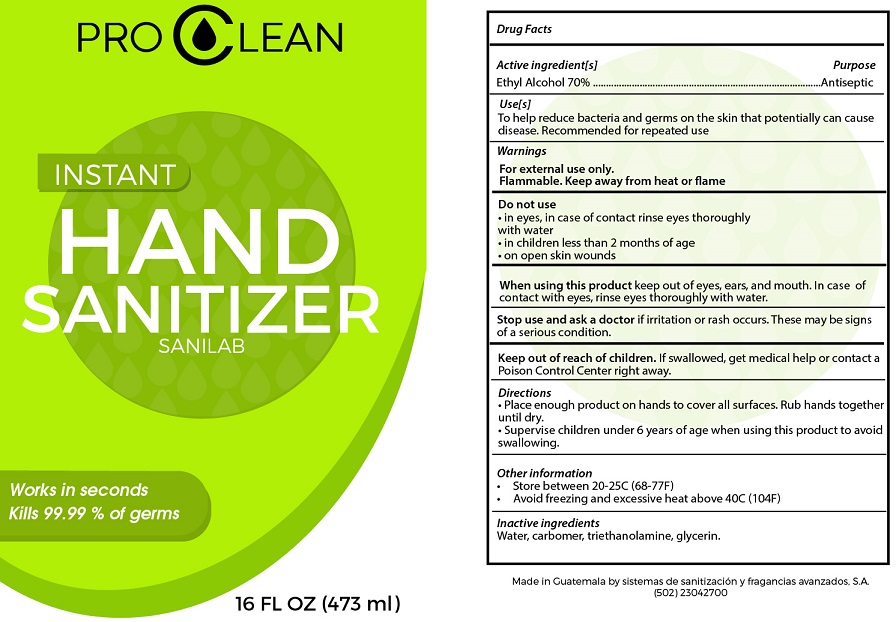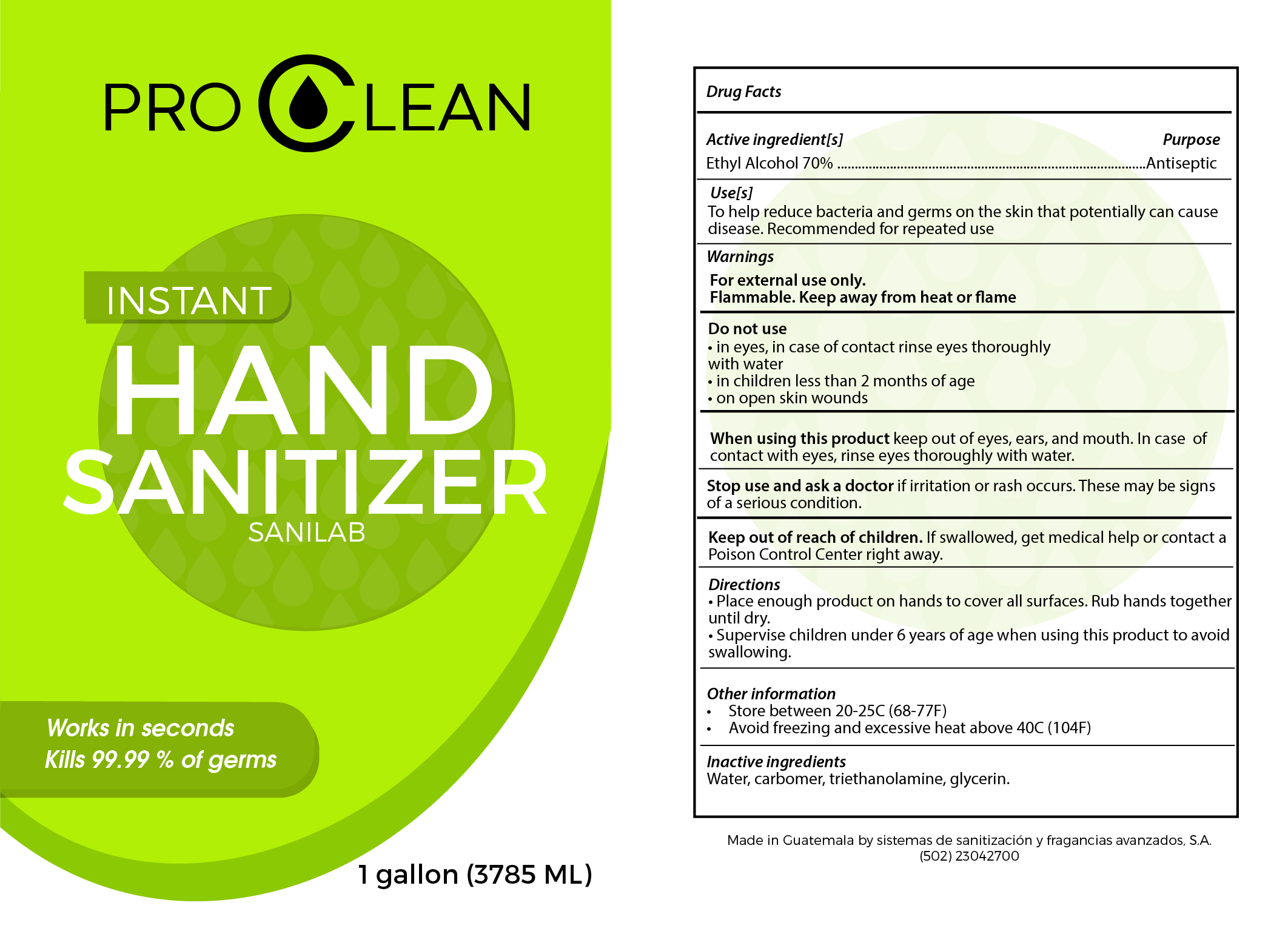 DRUG LABEL: Pro Clean Instant Hand Sanitizer
NDC: 80570-001 | Form: LIQUID
Manufacturer: Sistemas de Sanitazion y Fragancias Avanzados S.A.
Category: otc | Type: HUMAN OTC DRUG LABEL
Date: 20201202

ACTIVE INGREDIENTS: ALCOHOL 0.7 mL/1 mL
INACTIVE INGREDIENTS: WATER; CARBOMER HOMOPOLYMER, UNSPECIFIED TYPE; TROLAMINE; GLYCERIN

Pro Clean Instant Hand Sanitizer

Active ingredient[s]

Ethyl Alcohol 70%

Purpose

Antiseptic

Use[s]

To help reduce bacteria and germs on the skin that potentially can cuase disease. Recommended for repeated use

Warnings

For external use only.

Flammable. Keep away from heat or flame

Do not use

- in eyes, in case of contact rinse eyes thoroughly with water
- in children less than 2 months of age
- on open skin wounds

When using this product

keep out of eyes, ears, and mouth. In case of contact with eyes, rinse eyes thoroughly with water.

Stop use and ask a doctor

if irritation or rash occurs. These may be signs of a serious condition.

Keep out of reach of children.

If swallowed, get medical help or contact a Poison Control Center right away.

Directions

- Place enough product on hands to cover all surfaces. Rub hands together until dry.
- Supervise children under 6 years of age when using this product to avoid swallowing.

Other information

- Store between 20-25C (68-77F)
- Avoid freezing and excessive heat above 40C (104F)

Inactive ingredients

Water, carbomer, triethanolamine, glycerin.